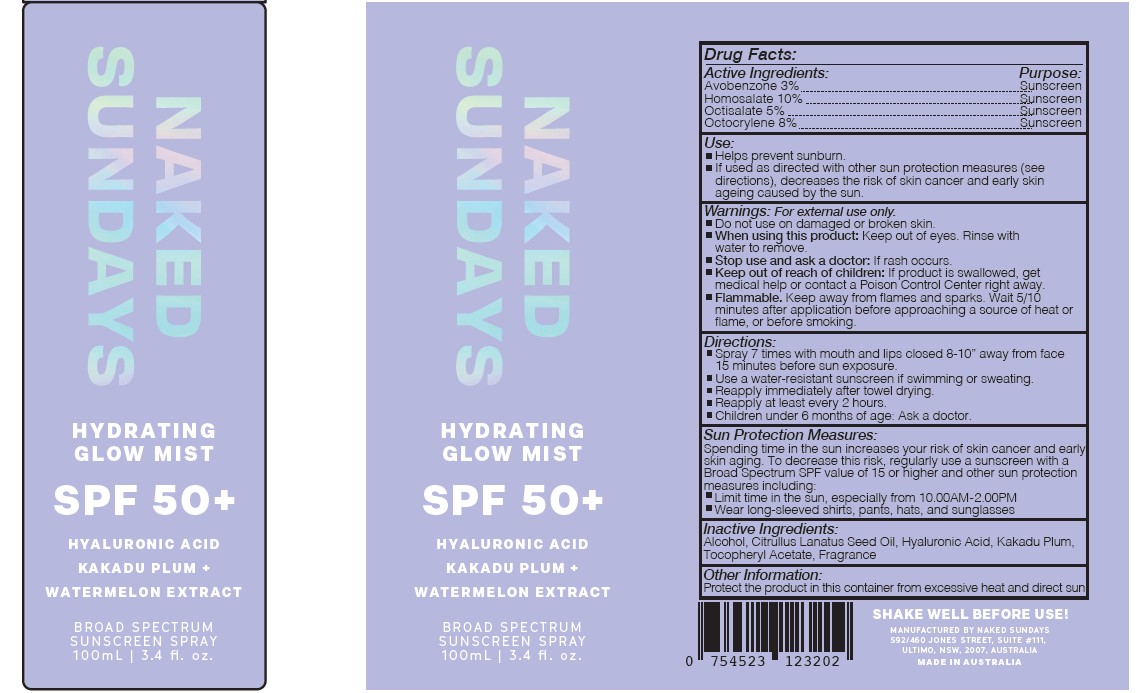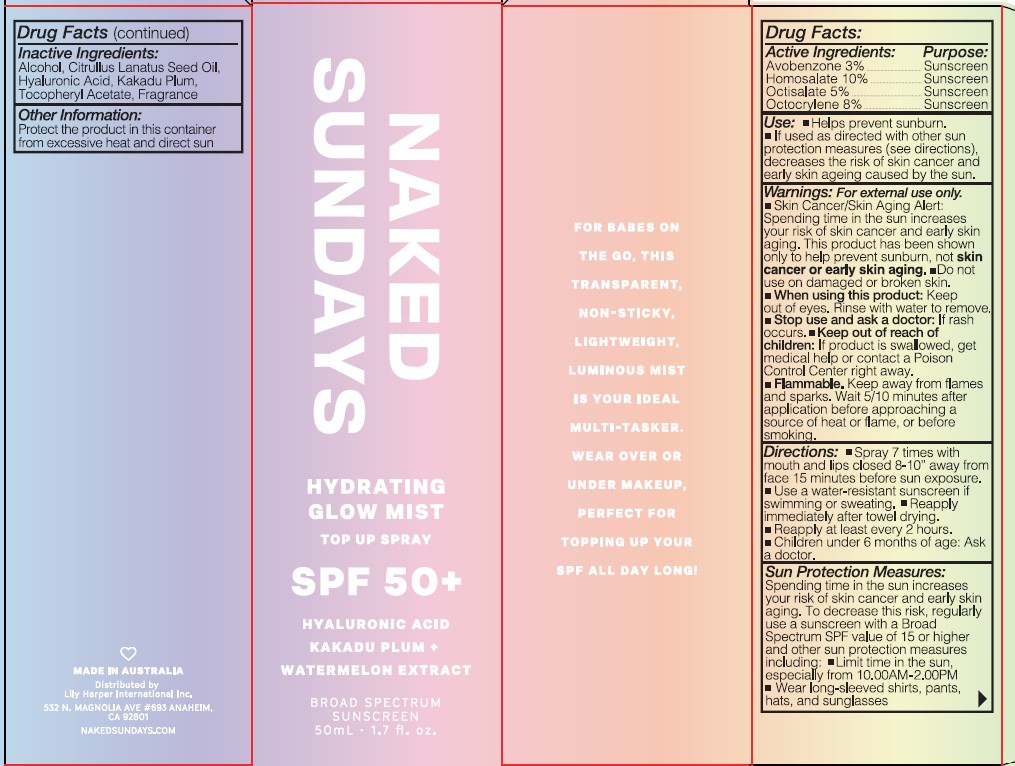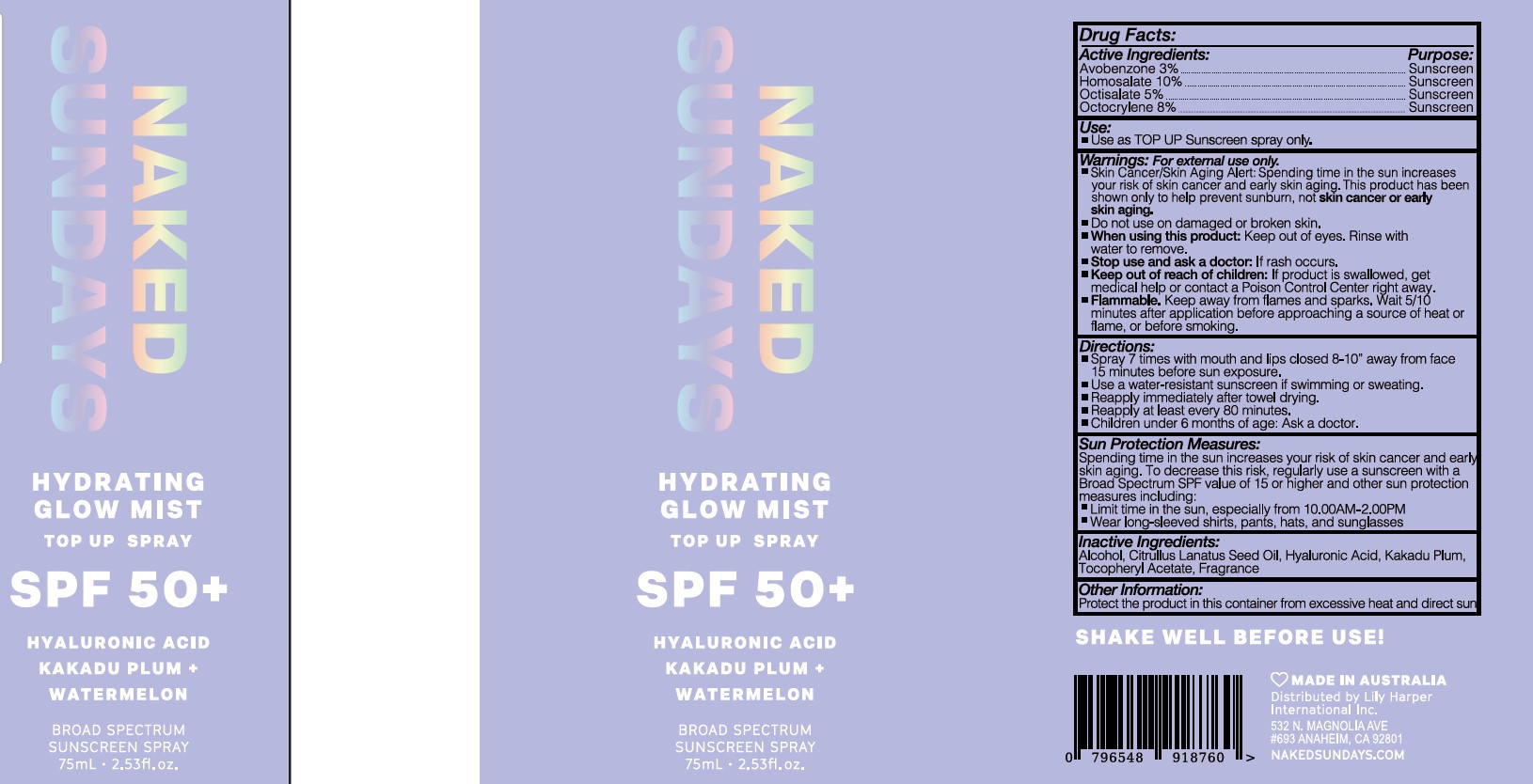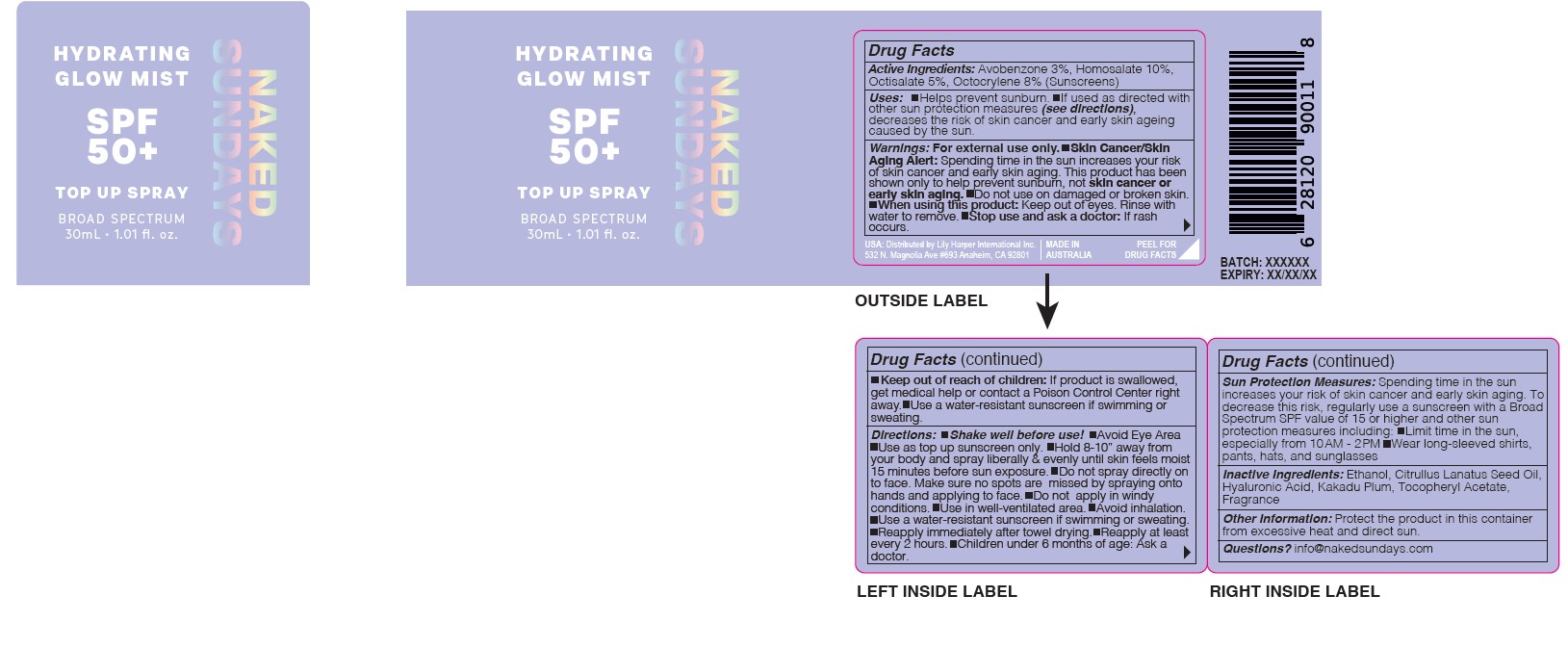 DRUG LABEL: HYDRATING GLOW MIST
NDC: 30807-6006 | Form: SPRAY
Manufacturer: WILD CHILD LABORATORIES PTY LTD
Category: otc | Type: HUMAN OTC DRUG LABEL
Date: 20251121

ACTIVE INGREDIENTS: AVOBENZONE 3 g/100 mL; HOMOSALATE 10 g/100 mL; OCTISALATE 5 g/100 mL; OCTOCRYLENE 8 g/100 mL
INACTIVE INGREDIENTS: BUTYLOCTYL SALICYLATE; .ALPHA.-TOCOPHEROL ACETATE; ALCOHOL; HYALURONIC ACID; KAKADU PLUM; WATERMELON

NAKED SUNDAYS HYDRATING GLOW MIST SPF 50

ACTIVE INGREDIENTS

Avobenzone 3%

Homosalate 10%

Octilsalate 5%

Octocrylene 8%

Purpose

Sunscreen

USES

- Helps prevent sunburn.
- If used as directed with other sun protection measures (see directions), decreases the risk of skin cancer and early skin ageing caused by the sun.

WARNINGS

For external use only.

- Do not use on damaged or broken skin.
- When using this product: keep out of eyes. Rinse with water to remove.
- Stop use and ask a doctor if: rash occurs.
- Keep out of reach of children: If product is swallowed, get medical help.

Keep out of reach of children. If product is swallowed, get medical help or contact a Poison Control Center right away.

DIRECTIONS

- SPRAY 7 TIMES WITH MOUTH AND LIPS CLOSED 8-10" AWAY FROM FACE 15 MINUTES BEFORE SUN EXPOSURE.
- Reapply after 80 minutes of swimming or sweating.
- Reapply immediately after towel drying.
- Reapply at least every 2 hours.
- Children under 3 years of age: Ask a doctor.

SUN PROTECTION MEASURES:

Spending time in the sun increases your risk of skin cancer and early skin aging. To decrease this risk, regularly use a sunscreen with a Broad Spectrum SPF value of 15 or higher and other sun protection measures including:

- Limit time in the sun, especially from 10.00AM - 2.00PM
- Wear long-sleeved shirts, pants, hats, and sunglasses

INACTIVE INGREDIENTS

Butyloctyl Salicylate, D-Alpha-tocopheryl acetate, Ethanol, Fragrance, Hyaluronic acid, Terminalia Ferdinandiana (Kakadu Plum), Citrulius lanatus fruit extract (Watermelon).

OTHER INFORMATION

Protect the product in this container from excessive heat and direct sun.